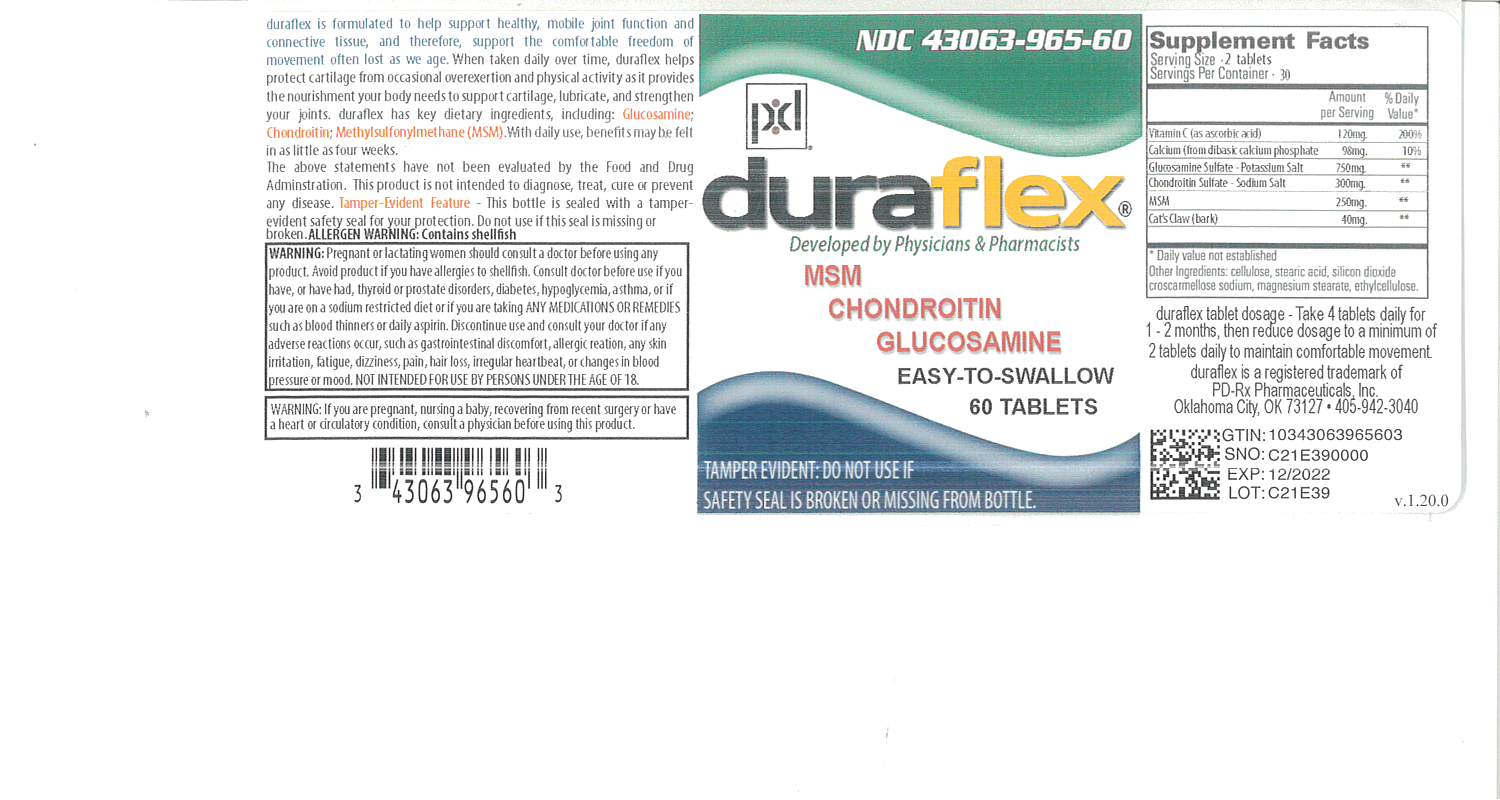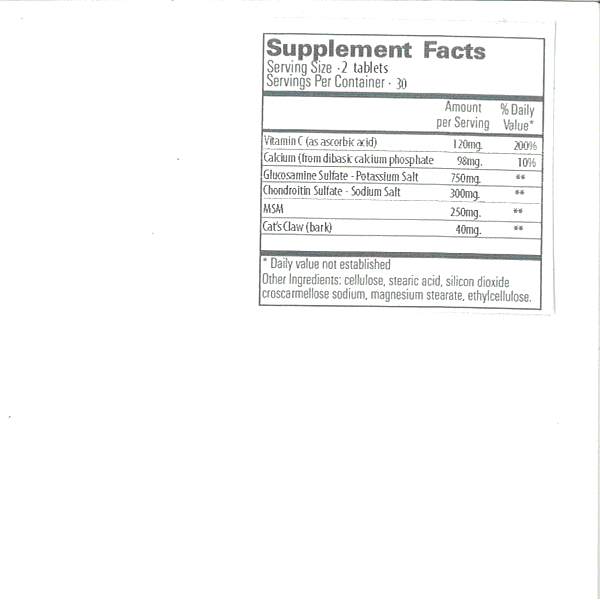 DRUG LABEL: duraflex
NDC: 43063-965 | Form: TABLET
Manufacturer: PD-Rx Pharmaceuticals, Inc.
Category: other | Type: DIETARY SUPPLEMENT
Date: 20210716

ACTIVE INGREDIENTS: ASCORBIC ACID 60 mg/1 1; DIBASIC CALCIUM PHOSPHATE DIHYDRATE 49 mg/1 1; CHONDROITIN SULFATE SODIUM (BOVINE) 150 mg/1 1; DIMETHYL SULFOXIDE 125 mg/1 1; CAT'S CLAW 175 mg/1 1
INACTIVE INGREDIENTS: GLUCOSAMINE SULFATE POTASSIUM CHLORIDE 375 mg/1 1; POWDERED CELLULOSE; STEARIC ACID; SILICON DIOXIDE; CROSCARMELLOSE SODIUM; MAGNESIUM STEARATE; ETHYLCELLULOSES

HEALTH CLAIM:

DURAFLEX TABLETS - Dietary Supplement

OTHER INGREDIENTS: cellulose, stearic acid, silicon dioxide, croscamellose sodium, magnesium stearate, ethycellose.

DESCRIPTION:

duraflex is formulated to help support healthy, mobile joint function and connective tissue, and therefore, support the comfortable freedom of movement often lost as we age. When taken daily over time, duraflex helps protect cartilage from occasional overexertion and physical activity as it provides the nourishment your body needs to support cartilage, lubricate, and strengthen your joints. duraflex has key dietary ingredients, including: Glucosamine; Chondroitin; Methylsulfonylmethane (MSM). With daily use, benefits may be felt in as little as four weels.†

† The above statements have not been evaluated by the Food and Drug Administration. This product is not intended to diagnose, treat, cure or prevent any disease.

WARNING AND PRECAUTIONS

Pregnant or lactating women should consult a doctor using any product. Avoid product if you have allergies to shellfish. Consult doctor before use if you have, or have had, thyroid or prostate disorders, diabetes, hypoglycemia, asthma, or if you are on a sodium restricted diet or if you are taking ANY MEDICATIONS OR REMEDIES such as blood thinners or daily aspirin. Discontinue use and consult your doctor before use if any adverse reactions occur, such as gastointestinal discomfort, allergic reaction, any skin irritation, fatigue, dizziness, pain, hair loss, irregular heartbeat, or changes in blood pressure or mood. NOT INTENDED FOR USE BY PERSONS UNDER THE AGE OF 18.

WARNING: If you are pregnant, nursing a baby, recovering from recent surgery or have a heart or circulatory condition, consult a physician before using this product.

ADVERSE REACTIONS

ALLERGEN WARNING: CONTAINS SHELLFISH

DOSAGE & ADMINISTRATION

duraflex tablet dosage- Take 4 tablets daily for 1-2 months, then reduce dosage to a minimum of 2 tablets daily to maintain comfortable movement

HOW SUPPLIED HEALTH CLAIM:

duraflex Dietary Supplement
tablets are brown
Bottles of 60 tablets NDC 43063-965-60
Bottles of 120 tablets NDC 43063-965-98‡

duraflex is a registered trademark of PD-Rx Pharmaceuticals, Inc. Oklahoma City, OK 73127 405-942-3040

STORAGE AND HANDLING:

Tamper-Evident Feature- This bottle is sealed with a tamperevident safety seal for your protection. Do not use if this seal is missing or broken.